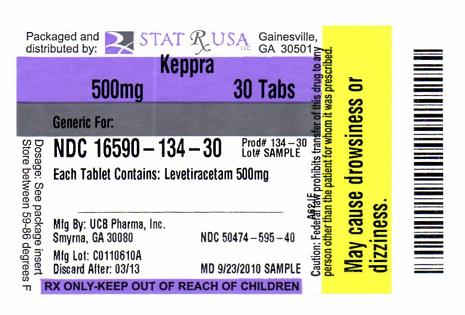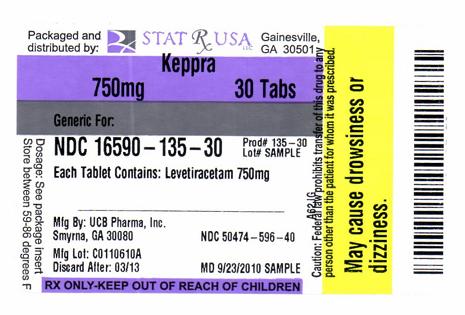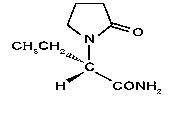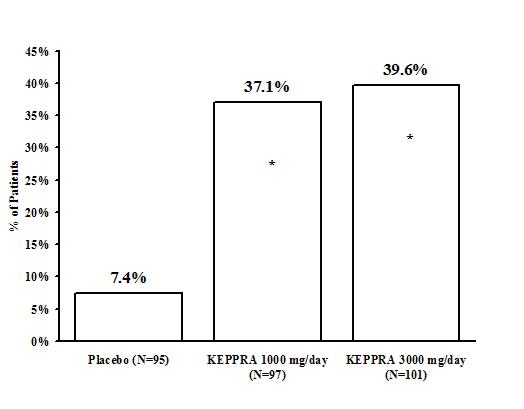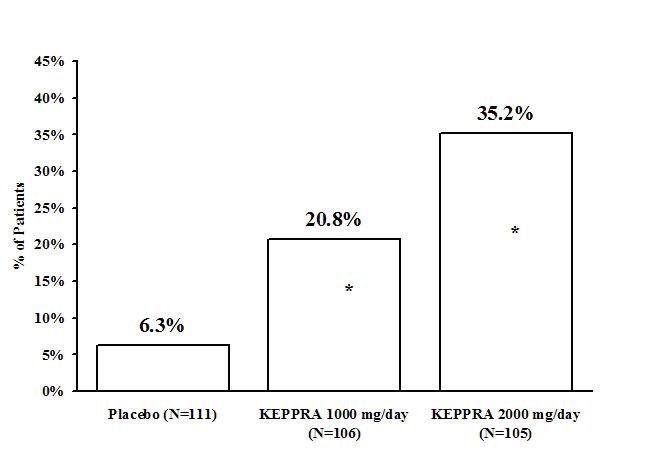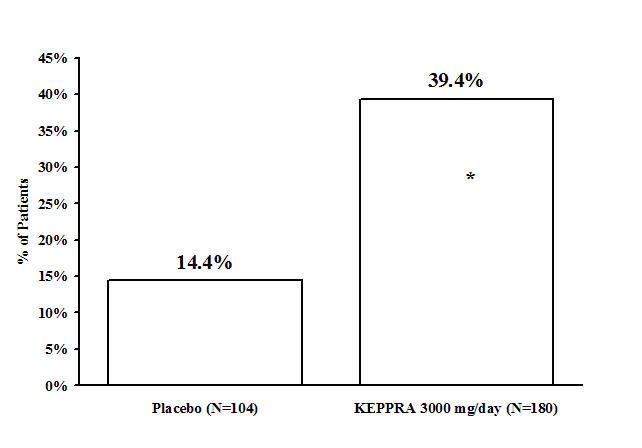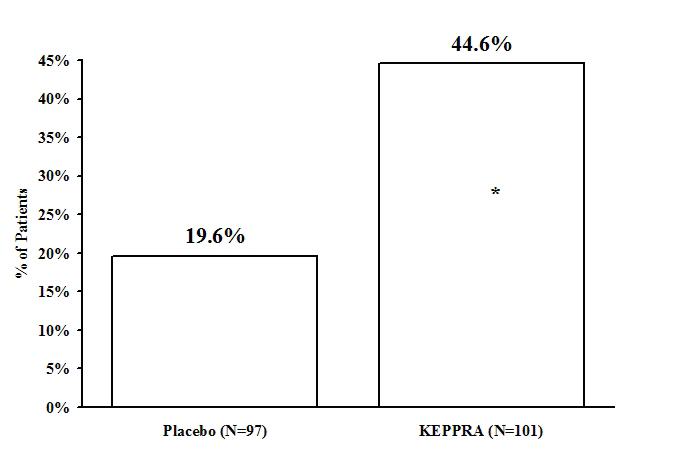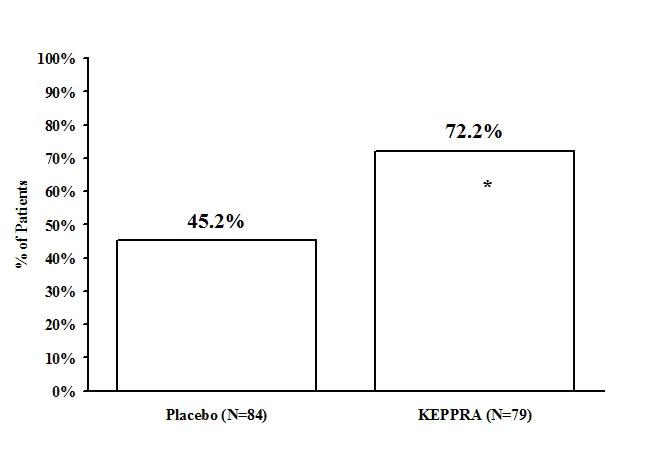 DRUG LABEL: KEPPRA
NDC: 16590-134 | Form: TABLET, FILM COATED
Manufacturer: STAT RX USA LLC
Category: prescription | Type: HUMAN PRESCRIPTION DRUG LABEL
Date: 20110323

ACTIVE INGREDIENTS: LEVETIRACETAM 500 mg/1 1
INACTIVE INGREDIENTS: SILICON DIOXIDE; CROSCARMELLOSE SODIUM; MAGNESIUM STEARATE; POLYETHYLENE GLYCOL 3350; POLYETHYLENE GLYCOL 6000; POLYVINYL ALCOHOL; TALC; TITANIUM DIOXIDE; FERRIC OXIDE YELLOW

DESCRIPTION

KEPPRA is an antiepileptic drug available as 250 mg (blue), 500 mg (yellow), 750 mg (orange), and 1000 mg (white) tablets and as a clear, colorless, grape-flavored liquid (100 mg/mL) for oral administration.

The chemical name of levetiracetam, a single enantiomer, is (-)-(S)-α-ethyl-2-oxo-1-pyrrolidine acetamide, its molecular formula is C8H14N2O2 and its molecular weight is 170.21. Levetiracetam is chemically unrelated to existing antiepileptic drugs (AEDs). It has the following structural formula:

Levetiracetam is a white to off-white crystalline powder with a faint odor and a bitter taste. It is very soluble in water (104.0 g/100 mL). It is freely soluble in chloroform (65.3 g/100 mL) and in methanol (53.6 g/100 mL), soluble in ethanol (16.5 g/100 mL), sparingly soluble in acetonitrile (5.7 g/100 mL) and practically insoluble in n-hexane. (Solubility limits are expressed as g/100 mL solvent.)

KEPPRA tablets contain the labeled amount of levetiracetam. Inactive ingredients: colloidal silicon dioxide, croscarmellose sodium, magnesium stearate, polyethylene glycol 3350, polyethylene glycol 6000, polyvinyl alcohol, talc, titanium dioxide, and additional agents listed below:

250 mg tablets: FD&C Blue #2/indigo carmine aluminum lake
500 mg tablets: iron oxide yellow
750 mg tablets: FD&C yellow #6/sunset yellow FCF aluminum lake, iron oxide red

KEPPRA oral solution contains 100 mg of levetiracetam per mL. Inactive ingredients: ammonium glycyrrhizinate, citric acid monohydrate, glycerin, maltitol solution, methylparaben, potassium acesulfame, propylparaben, purified water, sodium citrate dihydrate and natural and artificial flavor.

CLINICAL PHARMACOLOGY

Mechanism Of Action

The precise mechanism(s) by which levetiracetam exerts its antiepileptic effect is unknown. The antiepileptic activity of levetiracetam was assessed in a number of animal models of epileptic seizures. Levetiracetam did not inhibit single seizures induced by maximal stimulation with electrical current or different chemoconvulsants and showed only minimal activity in submaximal stimulation and in threshold tests. Protection was observed, however, against secondarily generalized activity from focal seizures induced by pilocarpine and kainic acid, two chemoconvulsants that induce seizures that mimic some features of human complex partial seizures with secondary generalization. Levetiracetam also displayed inhibitory properties in the kindling model in rats, another model of human complex partial seizures, both during kindling development and in the fully kindled state. The predictive value of these animal models for specific types of human epilepsy is uncertain.

In vitro and in vivo recordings of epileptiform activity from the hippocampus have shown that levetiracetam inhibits burst firing without affecting normal neuronal excitability, suggesting that levetiracetam may selectively prevent hypersynchronization of epileptiform burst firing and propagation of seizure activity.

Levetiracetam at concentrations of up to 10 µM did not demonstrate binding affinity for a variety of known receptors, such as those associated with benzodiazepines, GABA (gamma-aminobutyric acid), glycine, NMDA (N-methyl-D-aspartate), re-uptake sites, and second messenger systems. Furthermore, in vitro studies have failed to find an effect of levetiracetam on neuronal voltage-gated sodium or T-type calcium currents and levetiracetam does not appear to directly facilitate GABAergic neurotransmission. However, in vitro studies have demonstrated that levetiracetam opposes the activity of negative modulators of GABA- and glycine-gated currents and partially inhibits N-type calcium currents in neuronal cells.

A saturable and stereoselective neuronal binding site in rat brain tissue has been described for levetiracetam. Experimental data indicate that this binding site is the synaptic vesicle protein SV2A, thought to be involved in the regulation of vesicle exocytosis. Although the molecular significance of levetiracetam binding to synaptic vesicle protein SV2A is not understood, levetiracetam and related analogs showed a rank order of affinity for SV2A which correlated with the potency of their antiseizure activity in audiogenic seizure-prone mice. These findings suggest that the interaction of levetiracetam with the SV2A protein may contribute to the antiepileptic mechanism of action of the drug.

Pharmacokinetics

The pharmacokinetics of levetiracetam have been studied in healthy adult subjects, adults and pediatric patients with epilepsy, elderly subjects and subjects with renal and hepatic impairment.

Overview

Levetiracetam is rapidly and almost completely absorbed after oral administration. Levetiracetam tablets and oral solution are bioequivalent. The pharmacokinetics are linear and time-invariant, with low intra- and inter-subject variability. The extent of bioavailability of levetiracetam is not affected by food. Levetiracetam is not significantly protein-bound (<10% bound) and its volume of distribution is close to the volume of intracellular and extracellular water. Sixty-six percent (66%) of the dose is renally excreted unchanged. The major metabolic pathway of levetiracetam (24% of dose) is an enzymatic hydrolysis of the acetamide group. It is not liver cytochrome P450 dependent. The metabolites have no known pharmacological activity and are renally excreted. Plasma half-life of levetiracetam across studies is approximately 6-8 hours. It is increased in the elderly (primarily due to impaired renal clearance) and in subjects with renal impairment.

Absorption And Distribution

Absorption of levetiracetam is rapid, with peak plasma concentrations occurring in about an hour following oral administration in fasted subjects. The oral bioavailability of levetiracetam tablets is 100% and the tablets and oral solution are bioequivalent in rate and extent of absorption. Food does not affect the extent of absorption of levetiracetam but it decreases Cmax by 20% and delays Tmax by 1.5 hours. The pharmacokinetics of levetiracetam are linear over the dose range of 500-5000 mg. Steady state is achieved after 2 days of multiple twice-daily dosing. Levetiracetam and its major metabolite are less than 10% bound to plasma proteins; clinically significant interactions with other drugs through competition for protein binding sites are therefore unlikely.

Metabolism

Levetiracetam is not extensively metabolized in humans. The major metabolic pathway is the enzymatic hydrolysis of the acetamide group, which produces the carboxylic acid metabolite, ucb L057 (24% of dose) and is not dependent on any liver cytochrome P450 isoenzymes. The major metabolite is inactive in animal seizure models. Two minor metabolites were identified as the product of hydroxylation of the 2-oxo-pyrrolidine ring (2% of dose) and opening of the 2-oxo-pyrrolidine ring in position 5 (1% of dose). There is no enantiomeric interconversion of levetiracetam or its major metabolite.

Elimination

Levetiracetam plasma half-life in adults is 7 ± 1 hour and is unaffected by either dose or repeated administration. Levetiracetam is eliminated from the systemic circulation by renal excretion as unchanged drug which represents 66% of administered dose. The total body clearance is 0.96 mL/min/kg and the renal clearance is 0.6 mL/min/kg. The mechanism of excretion is glomerular filtration with subsequent partial tubular reabsorption. The metabolite ucb L057 is excreted by glomerular filtration and active tubular secretion with a renal clearance of 4 mL/min/kg. Levetiracetam elimination is correlated to creatinine clearance. Levetiracetam clearance is reduced in patients with impaired renal function (see Special Populations, Renal Impairment and DOSAGE AND ADMINISTRATION, Adult Patients with Impaired Renal Function).

Pharmacokinetic Interactions

In vitro data on metabolic interactions indicate that levetiracetam is unlikely to produce, or be subject to, pharmacokinetic interactions. Levetiracetam and its major metabolite, at concentrations well above Cmax levels achieved within the therapeutic dose range, are neither inhibitors of, nor high affinity substrates for, human liver cytochrome P450 isoforms, epoxide hydrolase or UDP-glucuronidation enzymes. In addition, levetiracetam does not affect the in vitro glucuronidation of valproic acid.

Potential pharmacokinetic interactions of or with levetiracetam were assessed in clinical pharmacokinetic studies (phenytoin, valproate, warfarin, digoxin, oral contraceptive, probenecid) and through pharmacokinetic screening in the placebo-controlled clinical studies in epilepsy patients (see PRECAUTIONS, Drug Interactions).

Special Populations

Elderly

Pharmacokinetics of levetiracetam were evaluated in 16 elderly subjects (age 61-88 years) with creatinine clearance ranging from 30 to 74 mL/min. Following oral administration of twice-daily dosing for 10 days, total body clearance decreased by 38% and the half-life was 2.5 hours longer in the elderly compared to healthy adults. This is most likely due to the decrease in renal function in these subjects.

Pediatric Patients

Pharmacokinetics of levetiracetam were evaluated in 24 pediatric patients (age 6-12 years) after single dose (20 mg/kg). The body weight adjusted apparent clearance of levetiracetam was approximately 40% higher than in adults.

A repeat dose pharmacokinetic study was conducted in pediatric patients (age 4-12 years) at doses of 20 mg/kg/day, 40 mg/kg/day, and 60 mg/kg/day. The evaluation of the pharmacokinetic profile of levetiracetam and its metabolite (ucb L057) in 14 pediatric patients demonstrated rapid absorption of levetiracetam at all doses with a Tmax of about 1 hour and a t½ of 5 hours across the three dosing levels. The pharmacokinetics of levetiracetam in children was linear between 20 to 60 mg/kg/day. The potential interaction of levetiracetam with other AEDs was also evaluated in these patients (see PRECAUTIONS, Drug Interactions). Levetiracetam had no significant effect on the plasma concentrations of carbamazepine, valproic acid, topiramate or lamotrigine. However, there was about a 22% increase of apparent clearance of levetiracetam when it was co-administered with an enzyme-inducing AED (e.g. carbamazepine). Population pharmacokinetic analysis showed that body weight was significantly correlated to clearance of levetiracetam in pediatric patients; clearance increased with an increase in body weight.

Gender

Levetiracetam Cmax and AUC were 20% higher in women (N=11) compared to men (N=12). However, clearances adjusted for body weight were comparable.

Race

Formal pharmacokinetic studies of the effects of race have not been conducted. Cross study comparisons involving Caucasians (N=12) and Asians (N=12), however, show that pharmacokinetics of levetiracetam were comparable between the two races. Because levetiracetam is primarily renally excreted and there are no important racial differences in creatinine clearance, pharmacokinetic differences due to race are not expected.

Renal Impairment

The disposition of levetiracetam was studied in adult subjects with varying degrees of renal function. Total body clearance of levetiracetam is reduced in patients with impaired renal function by 40% in the mild group (CLcr = 50-80 mL/min), 50% in the moderate group (CLcr = 30-50 mL/min) and 60% in the severe renal impairment group (CLcr <30 mL/min). Clearance of levetiracetam is correlated with creatinine clearance.

In anuric (end stage renal disease) patients, the total body clearance decreased 70% compared to normal subjects (CLcr >80mL/min). Approximately 50% of the pool of levetiracetam in the body is removed during a standard 4-hour hemodialysis procedure.

Dosage should be reduced in patients with impaired renal function receiving levetiracetam, and supplemental doses should be given to patients after dialysis (see PRECAUTIONS and DOSAGE AND ADMINISTRATION, Adult Patients With Impaired Renal Function).

Hepatic Impairment

In subjects with mild (Child-Pugh A) to moderate (Child-Pugh B) hepatic impairment, the pharmacokinetics of levetiracetam were unchanged. In patients with severe hepatic impairment (Child-Pugh C), total body clearance was 50% that of normal subjects, but decreased renal clearance accounted for most of the decrease. No dose adjustment is needed for patients with hepatic impairment.

CLINICAL STUDIES

In the following studies, statistical significance versus placebo indicates a p value < 0.05.

Effectiveness In Partial Onset Seizures In Adults With Epilepsy

The effectiveness of KEPPRA as adjunctive therapy (added to other antiepileptic drugs) in adults was established in three multicenter, randomized, double-blind, placebo-controlled clinical studies in patients who had refractory partial onset seizures with or without secondary generalization. The tablet formulation was used in all these studies. In these studies, 904 patients were randomized to placebo, 1000 mg, 2000 mg, or 3000 mg/day. Patients enrolled in Study 1 or Study 2 had refractory partial onset seizures for at least two years and had taken two or more classical AEDs. Patients enrolled in Study 3 had refractory partial onset seizures for at least 1 year and had taken one classical AED. At the time of the study, patients were taking a stable dose regimen of at least one and could take a maximum of two AEDs. During the baseline period, patients had to have experienced at least two partial onset seizures during each 4-week period.

Study 1

Study 1 was a double-blind, placebo-controlled, parallel-group study conducted at 41 sites in the United States comparing KEPPRA 1000 mg/day (N=97), KEPPRA 3000 mg/day (N=101), and placebo (N=95) given in equally divided doses twice daily. After a prospective baseline period of 12 weeks, patients were randomized to one of the three treatment groups described above. The 18-week treatment period consisted of a 6-week titration period, followed by a 12-week fixed dose evaluation period, during which concomitant AED regimens were held constant. The primary measure of effectiveness was a between group comparison of the percent reduction in weekly partial seizure frequency relative to placebo over the entire randomized treatment period (titration + evaluation period). Secondary outcome variables included the responder rate (incidence of patients with ≥50% reduction from baseline in partial onset seizure frequency). The results of the analysis of Study 1 are displayed in Table 1.

Table 1: Reduction In Mean Over Placebo In Weekly Frequency Of Partial Onset Seizures In Study 1
 | Placebo (N=95) | KEPPRA 1000 mg/day (N=97) | KEPPRA 3000 mg/day (N=101)
Percent reduction in partial seizure frequency over placebo | – | 26.1%* | 30.1%*
* statistically significant versus placebo

The percentage of patients (y-axis) who achieved ≥50% reduction in weekly seizure rates from baseline in partial onset seizure frequency over the entire randomized treatment period (titration + evaluation period) within the three treatment groups (x-axis) is presented in Figure 1.

Figure 1: Responder Rate (≥50% Reduction From Baseline) In Study 1
* statistically significant versus placebo

Study 2

Study 2 was a double-blind, placebo-controlled, crossover study conducted at 62 centers in Europe comparing KEPPRA 1000 mg/day (N=106), KEPPRA 2000 mg/day (N=105), and placebo (N=111) given in equally divided doses twice daily.

The first period of the study (Period A) was designed to be analyzed as a parallel-group study. After a prospective baseline period of up to 12 weeks, patients were randomized to one of the three treatment groups described above. The 16-week treatment period consisted of the 4-week titration period followed by a 12-week fixed dose evaluation period, during which concomitant AED regimens were held constant. The primary measure of effectiveness was a between group comparison of the percent reduction in weekly partial seizure frequency relative to placebo over the entire randomized treatment period (titration + evaluation period). Secondary outcome variables included the responder rate (incidence of patients with ≥50% reduction from baseline in partial onset seizure frequency). The results of the analysis of Period A are displayed in Table 2.

Table 2: Reduction In Mean Over Placebo In Weekly Frequency Of Partial Onset Seizures In Study 2: Period A
 | Placebo (N=111) | KEPPRA 1000 mg/day (N=106) | KEPPRA 2000 mg/day (N=105)
Percent reduction in partial seizure frequency over placebo | – | 17.1%* | 21.4%*
* statistically significant versus placebo

The percentage of patients (y-axis) who achieved ≥50% reduction in weekly seizure rates from baseline in partial onset seizure frequency over the entire randomized treatment period (titration + evaluation period) within the three treatment groups (x-axis) is presented in Figure 2.

Figure 2: Responder Rate (≥50% Reduction From Baseline) In Study 2: Period A
* statistically significant versus placebo

The comparison of KEPPRA 2000 mg/day to KEPPRA 1000 mg/day for responder rate was statistically significant (P=0.02). Analysis of the trial as a cross-over yielded similar results.

Study 3

Study 3 was a double-blind, placebo-controlled, parallel-group study conducted at 47 centers in Europe comparing KEPPRA 3000 mg/day (N=180) and placebo (N=104) in patients with refractory partial onset seizures, with or without secondary generalization, receiving only one concomitant AED. Study drug was given in two divided doses. After a prospective baseline period of 12 weeks, patients were randomized to one of two treatment groups described above. The 16-week treatment period consisted of a 4-week titration period, followed by a 12-week fixed dose evaluation period, during which concomitant AED doses were held constant. The primary measure of effectiveness was a between group comparison of the percent reduction in weekly seizure frequency relative to placebo over the entire randomized treatment period (titration + evaluation period). Secondary outcome variables included the responder rate (incidence of patients with ≥50% reduction from baseline in partial onset seizure frequency). Table 3 displays the results of the analysis of Study 3.

Table 3: Reduction In Mean Over Placebo In Weekly Frequency Of Partial Onset Seizures In Study 3
 | Placebo (N=104) | KEPPRA 3000 mg/day (N=180)
Percent reduction in partial seizure frequency over placebo | – | 23.0%*
* statistically significant versus placebo

The percentage of patients (y-axis) who achieved ≥50% reduction in weekly seizure rates from baseline in partial onset seizure frequency over the entire randomized treatment period (titration + evaluation period) within the two treatment groups (x-axis) is presented in Figure 3.

Figure 3: Responder Rate (≥50% Reduction From Baseline) In Study 3
* statistically significant versus placebo

Effectiveness In Partial Onset Seizures In Pediatric Patients With Epilepsy

The effectiveness of KEPPRA as adjunctive therapy (added to other antiepileptic drugs) in pediatric patients was established in one multicenter, randomized double-blind, placebo-controlled study, conducted at 60 sites in North America, in children 4 to 16 years of age with partial seizures uncontrolled by standard antiepileptic drugs (AEDs). Eligible patients on a stable dose of 1-2 AEDs, who still experienced at least 4 partial onset seizures during the 4 weeks prior to screening, as well as at least 4 partial onset seizures in each of the two 4-week baseline periods, were randomized to receive either KEPPRA or placebo. The enrolled population included 198 patients (KEPPRA N=101, placebo N=97) with refractory partial onset seizures, whether or not secondarily generalized. The study consisted of an 8-week baseline period and 4-week titration period followed by a 10-week evaluation period. Dosing was initiated at a dose of 20 mg/kg/day in two divided doses. During the treatment period, KEPPRA doses were adjusted in 20 mg/kg/day increments, at 2-week intervals to the target dose of 60 mg/kg/day. The primary measure of effectiveness was a between group comparison of the percent reduction in weekly partial seizure frequency relative to placebo over the entire 14-week randomized treatment period (titration + evaluation period). Secondary outcome variables included the responder rate (incidence of patients with ≥ 50% reduction from baseline in partial onset seizure frequency per week). Table 4 displays the results of this study.

Table 4: Reduction In Mean Over Placebo In Weekly Frequency Of Partial Onset Seizures
 | Placebo (N=97) | KEPPRA (N=101)
Percent reduction in partial seizure frequency over placebo | – | 26.8%*
* statistically significant versus placebo

The percentage of patients (y-axis) who achieved ≥ 50% reduction in weekly seizure rates from baseline in partial onset seizure frequency over the entire randomized treatment period (titration + evaluation period) within the two treatment groups (x-axis) is presented in Figure 4.

Figure 4: Responder Rate (≥ 50% Reduction From Baseline)
* statistically significant versus placebo

Effectiveness In Myoclonic Seizures In Patients ≥12 Years Of Age With Juvenile Myoclonic Epilepsy (JME)

The effectiveness of KEPPRA as adjunctive therapy (added to other antiepileptic drugs) in patients 12 years of age and older with juvenile myoclonic epilepsy (JME) experiencing myoclonic seizures was established in one multicenter, randomized, double-blind, placebo-controlled study, conducted at 37 sites in 14 countries. Of the 120 patients enrolled, 113 had a diagnosis of confirmed or suspected JME. Eligible patients on a stable dose of 1 antiepileptic drug (AED) experiencing one or more myoclonic seizures per day for at least 8 days during the prospective 8-week baseline period were randomized to either KEPPRA or placebo (KEPPRA N=60, placebo N=60). Patients were titrated over 4 weeks to a target dose of 3000 mg/day and treated at a stable dose of 3000 mg/day over 12 weeks (evaluation period). Study drug was given in 2 divided doses.

The primary measure of effectiveness was the proportion of patients with at least 50% reduction in the number of days per week with one or more myoclonic seizures during the treatment period (titration + evaluation periods) as compared to baseline. Table 5 displays the results for the 113 patients with JME in this study.

Table 5: Responder Rate (≥50% Reduction From Baseline) In Myoclonic Seizure Days Per Week for Patients with JME
 | Placebo (N=59) | KEPPRA (N=54)
Percentage of responders | 23.7% | 60.4%*
* statistically significant versus placebo

Effectiveness For Primary Generalized Tonic-Clonic Seizures In Patients ≥6 Years Of Age

The effectiveness of KEPPRA as adjunctive therapy (added to other antiepileptic drugs) in patients 6 years of age and older with idiopathic generalized epilepsy experiencing primary generalized tonic-clonic (PGTC) seizures was established in one multicenter, randomized, double-blind, placebo-controlled study, conducted at 50 sites in 8 countries. Eligible patients on a stable dose of 1 or 2 antiepileptic drugs (AEDs) experiencing at least 3 PGTC seizures during the 8-week combined baseline period (at least one PGTC seizure during the 4 weeks prior to the prospective baseline period and at least one PGTC seizure during the 4-week prospective baseline period) were randomized to either KEPPRA or placebo. The 8-week combined baseline period is referred to as "baseline" in the remainder of this section. The population included 164 patients (KEPPRA N=80, placebo N=84) with idiopathic generalized epilepsy (predominately juvenile myoclonic epilepsy, juvenile absence epilepsy, childhood absence epilepsy, or epilepsy with Grand Mal seizures on awakening) experiencing primary generalized tonic-clonic seizures. Each of these syndromes of idiopathic generalized epilepsy was well represented in this patient population. Patients were titrated over 4 weeks to a target dose of 3000 mg/day for adults or a pediatric target dose of 60 mg/kg/day and treated at a stable dose of 3000 mg/day (or 60 mg/kg/day for children) over 20 weeks (evaluation period). Study drug was given in 2 equally divided doses per day.

The primary measure of effectiveness was the percent reduction from baseline in weekly PGTC seizure frequency for KEPPRA and placebo treatment groups over the treatment period (titration + evaluation periods). There was a statistically significant decrease from baseline in PGTC frequency in the KEPPRA-treated patients compared to the placebo-treated patients.

Table 6: Median Percent Reduction From Baseline In PGTC Seizure Frequency Per Week
 | Placebo (N=84) | KEPPRA (N=78)
Percent reduction in PGTC seizure frequency | 44.6% | 77.6%*
* statistically significant versus placebo

The percentage of patients (y-axis) who achieved ≥50% reduction in weekly seizure rates from baseline in PGTC seizure frequency over the entire randomized treatment period (titration + evaluation period) within the two treatment groups (x-axis) is presented in Figure 5.

Figure 5: Responder Rate (≥50% Reduction From Baseline) In PGTC Seizure Frequency Per Week
* statistically significant versus placebo

INDICATIONS AND USAGE

KEPPRA is indicated as adjunctive therapy in the treatment of partial onset seizures in adults and children 4 years of age and older with epilepsy.

KEPPRA is indicated as adjunctive therapy in the treatment of myoclonic seizures in adults and adolescents 12 years of age and older with juvenile myoclonic epilepsy.

KEPPRA is indicated as adjunctive therapy in the treatment of primary generalized tonic-clonic seizures in adults and children 6 years of age and older with idiopathic generalized epilepsy.

CONTRAINDICATIONS

This product should not be administered to patients who have previously exhibited hypersensitivity to levetiracetam or any of the inactive ingredients in KEPPRA tablets or oral solution.

WARNINGS

Suicidal Behavior and Ideation

Antiepileptic drugs (AEDs), including KEPPRA, increase the risk of suicidal thoughts or behavior in patients taking these drugs for any indication. Patients treated with any AED for any indication should be monitored for the emergence or worsening of depression, suicidal thoughts or behavior, and/or any unusual changes in mood or behavior.

Pooled analyses of 199 placebo-controlled clinical trials (mono- and adjunctive therapy) of 11 different AEDs showed that patients randomized to one of the AEDs had approximately twice the risk (adjusted Relative Risk 1.8, 95% CI:1.2, 2.7) of suicidal thinking or behavior compared to patients randomized to placebo. In these trials, which had a median treatment duration of 12 weeks, the estimated incidence rate of suicidal behavior or ideation among 27,863 AED-treated patients was 0.43%, compared to 0.24% among 16,029 placebo-treated patients, representing an increase of approximately one case of suicidal thinking or behavior for every 530 patients treated. There were four suicides in drug-treated patients in the trials and none in placebo-treated patients, but the number is too small to allow any conclusion about drug effect on suicide.

The increased risk of suicidal thoughts or behavior with AEDs was observed as early as one week after starting drug treatment with AEDs and persisted for the duration of treatment assessed. Because most trials included in the analysis did not extend beyond 24 weeks, the risk of suicidal thoughts or behavior beyond 24 weeks could not be assessed.

The risk of suicidal thoughts or behavior was generally consistent among drugs in the data analyzed. The finding of increased risk with AEDs of varying mechanisms of action and across a range of indications suggests that the risk applies to all AEDs used for any indication. The risk did not vary substantially by age (5-100 years) in the clinical trials analyzed. Table 7 shows absolute and relative risk by indication for all evaluated AEDs.

Table 7 Risk by indication for antiepileptic drugs in the pooled analysis
Indication | Placebo Patients with Events Per 1000 Patients | Drug Patients with Events Per 1000 Patients | Relative Risk: Incidence of Events in Drug Patients/Incidence in Placebo Patients | Risk Difference: Additional Drug Patients with Events Per 1000 Patients
Epilepsy | 1.0 | 3.4 | 3.5 | 2.4
Psychiatric | 5.7 | 8.5 | 1.5 | 2.9
Other | 1.0 | 1.8 | 1.9 | 0.9
Total | 2.4 | 4.3 | 1.8 | 1.9

The relative risk for suicidal thoughts or behavior was higher in clinical trials for epilepsy than in clinical trials for psychiatric or other conditions, but the absolute risk differences were similar for the epilepsy and psychiatric indications.

Anyone considering prescribing KEPPRA or any other AED must balance the risk of suicidal thoughts or behaviors with the risk of untreated illness. Epilepsy and many other illnesses for which AEDs are prescribed are themselves associated with morbidity and mortality and an increased risk of suicidal thoughts and behavior. Should suicidal thoughts and behavior emerge during treatment, the prescriber needs to consider whether the emergence of these symptoms in any given patient may be related to the illness being treated.

Patients, their caregivers, and families should be informed that AEDs increase the risk of suicidal thoughts and behavior and should be advised of the need to be alert for the emergence or worsening of the signs and symptoms of depression, any unusual changes in mood or behavior, or the emergence of suicidal thoughts, behavior, or thoughts about self-harm. Behaviors of concern should be reported immediately to healthcare providers.

Neuropsychiatric Adverse Events

Partial Onset Seizures

Adults

In adults experiencing partial onset seizures, KEPPRA use is associated with the occurrence of central nervous system adverse events that can be classified into the following categories: 1) somnolence and fatigue, 2) coordination difficulties, and 3) behavioral abnormalities.

In controlled trials of adult patients with epilepsy experiencing partial onset seizures, 14.8% of KEPPRA-treated patients reported somnolence, compared to 8.4% of placebo patients. There was no clear dose response up to 3000 mg/day. In a study where there was no titration, about 45% of patients receiving 4000 mg/day reported somnolence. The somnolence was considered serious in 0.3% of the treated patients, compared to 0% in the placebo group. About 3% of KEPPRA-treated patients discontinued treatment due to somnolence, compared to 0.7% of placebo patients. In 1.4% of treated patients and in 0.9% of placebo patients the dose was reduced, while 0.3% of the treated patients were hospitalized due to somnolence.

In controlled trials of adult patients with epilepsy experiencing partial onset seizures, 14.7% of treated patients reported asthenia, compared to 9.1% of placebo patients. Treatment was discontinued in 0.8% of treated patients as compared to 0.5% of placebo patients. In 0.5% of treated patients and in 0.2% of placebo patients the dose was reduced.

A total of 3.4% of KEPPRA-treated patients experienced coordination difficulties, (reported as either ataxia, abnormal gait, or incoordination) compared to 1.6% of placebo patients. A total of 0.4% of patients in controlled trials discontinued KEPPRA treatment due to ataxia, compared to 0% of placebo patients. In 0.7% of treated patients and in 0.2% of placebo patients the dose was reduced due to coordination difficulties, while one of the treated patients was hospitalized due to worsening of pre-existing ataxia.

Somnolence, asthenia and coordination difficulties occurred most frequently within the first 4 weeks of treatment.

In controlled trials of patients with epilepsy experiencing partial onset seizures, 5 (0.7%) of KEPPRA-treated patients experienced psychotic symptoms compared to 1 (0.2%) placebo patient. Two (0.3%) KEPPRA-treated patients were hospitalized and their treatment was discontinued. Both events, reported as psychosis, developed within the first week of treatment and resolved within 1 to 2 weeks following treatment discontinuation. Two other events, reported as hallucinations, occurred after 1-5 months and resolved within 2-7 days while the patients remained on treatment. In one patient experiencing psychotic depression occurring within a month, symptoms resolved within 45 days while the patient continued treatment. A total of 13.3% of KEPPRA patients experienced other behavioral symptoms (reported as aggression, agitation, anger, anxiety, apathy, depersonalization, depression, emotional lability, hostility, irritability, etc.) compared to 6.2% of placebo patients. Approximately half of these patients reported these events within the first 4 weeks. A total of 1.7% of treated patients discontinued treatment due to these events, compared to 0.2% of placebo patients. The treatment dose was reduced in 0.8% of treated patients and in 0.5% of placebo patients. A total of 0.8% of treated patients had a serious behavioral event (compared to 0.2% of placebo patients) and were hospitalized.

Pediatric Patients

In pediatric patients experiencing partial onset seizures, KEPPRA is associated with somnolence, fatigue, and behavioral abnormalities.

In the double-blind, controlled trial in children with epilepsy experiencing partial onset seizures, 22.8% of KEPPRA-treated patients experienced somnolence, compared to 11.3% of placebo patients. The design of the study prevented accurately assessing dose-response effects. No patient discontinued treatment for somnolence. In about 3.0% of KEPPRA-treated patients and in 3.1% of placebo patients the dose was reduced as a result of somnolence.

Asthenia was reported in 8.9% of KEPPRA-treated patients, compared to 3.1% of placebo patients. No patient discontinued treatment for asthenia, but asthenia led to a dose reduction in 3.0% of KEPPRA-treated patients compared to 0% of placebo patients.

A total of 37.6% of the KEPPRA-treated patients experienced behavioral symptoms (reported as agitation, anxiety, apathy, depersonalization, depression, emotional lability, hostility, hyperkinesia, nervousness, neurosis, and personality disorder), compared to 18.6% of placebo patients. Hostility was reported in 11.9% of KEPPRA-treated patients, compared to 6.2% of placebo patients. Nervousness was reported in 9.9% of KEPPRA-treated patients, compared to 2.1% of placebo patients. Depression was reported in 3.0% of KEPPRA-treated patients, compared to 1.0% of placebo patients.

A total of 3.0% of KEPPRA-treated patients discontinued treatment due to psychotic and nonpsychotic adverse events, compared to 4.1% of placebo patients. Overall, 10.9% of KEPPRA-treated patients experienced behavioral symptoms associated with discontinuation or dose reduction, compared to 6.2% of placebo patients.

Myoclonic Seizures

During clinical development, the number of patients with myoclonic seizures exposed to KEPPRA was considerably smaller than the number with partial seizures. Therefore, under-reporting of certain adverse events was more likely to occur in the myoclonic seizure population. In adult and adolescent patients experiencing myoclonic seizures, KEPPRA is associated with somnolence and behavioral abnormalities. It is expected that the events seen in partial seizure patients would occur in patients with JME.

In the double-blind, controlled trial in adults and adolescents with juvenile myoclonic epilepsy experiencing myoclonic seizures, 11.7% of KEPPRA-treated patients experienced somnolence compared to 1.7% of placebo patients. No patient discontinued treatment as a result of somnolence. In 1.7% of KEPPRA-treated patients and in 0% of placebo patients the dose was reduced as a result of somnolence.

Non-psychotic behavioral disorders (reported as aggression and irritability) occurred in 5% of the KEPPRA-treated patients compared to 0% of placebo patients. Non-psychotic mood disorders (reported as depressed mood, depression, and mood swings) occurred in 6.7% of KEPPRA-treated patients compared to 3.3% of placebo patients. A total of 5.0% of KEPPRA-treated patients had a reduction in dose or discontinued treatment due to behavioral or psychiatric events (reported as anxiety, depressed mood, depression, irritability, and nervousness), compared to 1.7% of placebo patients.

Primary Generalized Tonic-Clonic Seizures

During clinical development, the number of patients with primary generalized tonic-clonic epilepsy exposed to KEPPRA was considerably smaller than the number with partial epilepsy, described above. As in the partial seizure patients, behavioral symptoms appeared to be associated with KEPPRA treatment. Gait disorders and somnolence were also described in the study in primary generalized seizures, but with no difference between placebo and KEPPRA treatment groups and no appreciable discontinuations. Although it may be expected that drug related events seen in partial seizure patients would be seen in primary generalized epilepsy patients (e.g. somnolence and gait disturbance), these events may not have been observed because of the smaller sample size.

In patients 6 years of age and older experiencing primary generalized tonic-clonic seizures, KEPPRA is associated with behavioral abnormalities.

In the double-blind, controlled trial in patients with idiopathic generalized epilepsy experiencing primary generalized tonic-clonic seizures, irritability was the most frequently reported psychiatric adverse event occurring in 6.3% of KEPPRA-treated patients compared to 2.4% of placebo patients. Additionally, non-psychotic behavioral disorders (reported as abnormal behavior, aggression, conduct disorder, and irritability) occurred in 11.4% of the KEPPRA-treated patients compared to 3.6% of placebo patients. Of the KEPPRA-treated patients experiencing non-psychotic behavioral disorders, one patient discontinued treatment due to aggression. Non-psychotic mood disorders (including anger, apathy, depression, mood altered, mood swings, negativism, and tearfulness) occurred in 12.7% of KEPPRA-treated patients compared to 8.3% of placebo patients. No KEPPRA-treated patients discontinued or had a dose reduction as a result of these events. One patient experienced delusional behavior that required the lowering of the dose of KEPPRA.

In a long-term open label study that examined patients with various forms of primary generalized epilepsy, along with the non-psychotic behavioral disorders, 2 of 192 patients studied exhibited psychotic-like behavior. Behavior in one case was characterized by auditory hallucinations and suicidal thoughts and led to KEPPRA discontinuation. The other case was described as worsening of pre-existent schizophrenia and did not lead to drug discontinuation.

Withdrawal Seizures

Antiepileptic drugs, including KEPPRA, should be withdrawn gradually to minimize the potential of increased seizure frequency.

PRECAUTIONS

Hematologic Abnormalities

Partial Onset Seizures

Adults

Minor, but statistically significant, decreases compared to placebo in total mean RBC count (0.03 x 10^6/mm^3), mean hemoglobin (0.09 g/dL), and mean hematocrit (0.38%), were seen in KEPPRA-treated patients in controlled trials.

A total of 3.2% of treated and 1.8% of placebo patients had at least one possibly significant (≤2.8 x 10^9/L) decreased WBC, and 2.4% of treated and 1.4% of placebo patients had at least one possibly significant (≤1.0 x 10^9/L) decreased neutrophil count. Of the treated patients with a low neutrophil count, all but one rose towards or to baseline with continued treatment. No patient was discontinued secondary to low neutrophil counts.

Pediatric Patients

Minor, but statistically significant, decreases in WBC and neutrophil counts were seen in KEPPRA-treated patients as compared to placebo. The mean decreases from baseline in the KEPPRA-treated group were -0.4 × 10^9/L and -0.3 × 10^9/L, respectively, whereas there were small increases in the placebo group. Mean relative lymphocyte counts increased by 1.7% in KEPPRA-treated patients, compared to a decrease of 4% in placebo patients (statistically significant).

In the well-controlled trial, more KEPPRA-treated patients had a possibly clinically significant abnormally low WBC value (3.0% KEPPRA-treated versus 0% placebo), however, there was no apparent difference between treatment groups with respect to neutrophil count (5.0% KEPPRA-treated versus 4.2% placebo). No patient was discontinued secondary to low WBC or neutrophil counts.

Juvenile Myoclonic Epilepsy

Although there were no obvious hematologic abnormalities observed in patients with JME, the limited number of patients makes any conclusion tentative. The data from the partial seizure patients should be considered to be relevant for JME patients.

Hepatic Abnormalities

There were no meaningful changes in mean liver function tests (LFT) in controlled trials in adult or pediatric patients; lesser LFT abnormalities were similar in drug and placebo treated patients in controlled trials (1.4%). No adult or pediatric patients were discontinued from controlled trials for LFT abnormalities except for 1 (0.07%) adult epilepsy patient receiving open treatment.

Information For Patients

Patients and caregivers should be informed of the availability of a Medication Guide, and they should be instructed to read the Medication Guide prior to taking KEPPRA. The Medication Guide may also be found in the full prescribing information for KEPPRA posted on http://www.ucb-usa.com or by calling 1-866-822-0068. Patients should be instructed to take KEPPRA only as prescribed.

Patients, their caregivers, and families should be counseled that AEDs, including KEPPRA, may increase the risk of suicidal thoughts and behavior and should be advised of the need to be alert for the emergence or worsening of symptoms of depression, any unusual changes in mood or behavior, or the emergence of suicidal thoughts, behavior, or thoughts about self-harm. Behaviors of concern should be reported immediately to healthcare providers.

Patients should be advised that KEPPRA may cause changes in behavior (e.g. aggression, agitation, anger, anxiety, apathy, depression, hostility, and irritability) and in rare cases patients may experience psychotic symptoms.

Patients should be advised to notify their physician if they become pregnant or intend to become pregnant during therapy. Patients should be encouraged to enroll in the North American Antiepileptic Drug (NAAED) pregnancy registry if they become pregnant. This registry is collecting information about the safety of antiepileptic drugs during pregnancy. To enroll, patients can call the toll free number 1-888-233-2334. UCB, Inc. has established the UCB AED Pregnancy Registry to advance scientific knowledge about safety and outcomes associated with pregnant women being treated with all UCB antiepileptic drugs, including KEPPRA. To ensure broad program access and reach, either a healthcare provider or the patient can initiate enrollment in the UCB AED Pregnancy Registry by calling (888) 537-7734 (toll free) (See Pregnancy Section).

Patients should be advised that KEPPRA may cause dizziness and somnolence. Accordingly, patients should be advised not to drive or operate machinery or engage in other hazardous activities until they have gained sufficient experience on KEPPRA to gauge whether it adversely affects their performance of these activities.

Laboratory Tests

Although most laboratory tests are not systematically altered with KEPPRA treatment, there have been relatively infrequent abnormalities seen in hematologic parameters and liver function tests.

Drug Interactions

In vitro data on metabolic interactions indicate that KEPPRA is unlikely to produce, or be subject to, pharmacokinetic interactions. Levetiracetam and its major metabolite, at concentrations well above Cmax levels achieved within the therapeutic dose range, are neither inhibitors of nor high affinity substrates for human liver cytochrome P450 isoforms, epoxide hydrolase or UDP-glucuronidation enzymes. In addition, levetiracetam does not affect the in vitro glucuronidation of valproic acid.

Levetiracetam circulates largely unbound (<10% bound) to plasma proteins; clinically significant interactions with other drugs through competition for protein binding sites are therefore unlikely.

Potential pharmacokinetic interactions were assessed in clinical pharmacokinetic studies (phenytoin, valproate, oral contraceptive, digoxin, warfarin, probenecid) and through pharmacokinetic screening in the placebo-controlled clinical studies in epilepsy patients.

Drug-Drug Interactions Between KEPPRA And Other Antiepileptic Drugs (AEDs)

Phenytoin

KEPPRA (3000 mg daily) had no effect on the pharmacokinetic disposition of phenytoin in patients with refractory epilepsy. Pharmacokinetics of levetiracetam were also not affected by phenytoin.

Valproate

KEPPRA (1500 mg twice daily) did not alter the pharmacokinetics of valproate in healthy volunteers. Valproate 500 mg twice daily did not modify the rate or extent of levetiracetam absorption or its plasma clearance or urinary excretion. There also was no effect on exposure to and the excretion of the primary metabolite, ucb L057.

Potential drug interactions between KEPPRA and other AEDs (carbamazepine, gabapentin, lamotrigine, phenobarbital, phenytoin, primidone and valproate) were also assessed by evaluating the serum concentrations of levetiracetam and these AEDs during placebo-controlled clinical studies. These data indicate that levetiracetam does not influence the plasma concentration of other AEDs and that these AEDs do not influence the pharmacokinetics of levetiracetam.

Effect Of AEDs In Pediatric Patients

There was about a 22% increase of apparent total body clearance of levetiracetam when it was co-administered with enzyme-inducing AEDs. Dose adjustment is not recommended. Levetiracetam had no effect on plasma concentrations of carbamazepine, valproate, topiramate, or lamotrigine.

Other Drug Interactions

Oral Contraceptives

KEPPRA (500 mg twice daily) did not influence the pharmacokinetics of an oral contraceptive containing 0.03 mg ethinyl estradiol and 0.15 mg levonorgestrel, or of the luteinizing hormone and progesterone levels, indicating that impairment of contraceptive efficacy is unlikely. Coadministration of this oral contraceptive did not influence the pharmacokinetics of levetiracetam.

Digoxin

KEPPRA (1000 mg twice daily) did not influence the pharmacokinetics and pharmacodynamics (ECG) of digoxin given as a 0.25 mg dose every day. Coadministration of digoxin did not influence the pharmacokinetics of levetiracetam.

Warfarin

KEPPRA (1000 mg twice daily) did not influence the pharmacokinetics of R and S warfarin. Prothrombin time was not affected by levetiracetam. Coadministration of warfarin did not affect the pharmacokinetics of levetiracetam.

Probenecid

Probenecid, a renal tubular secretion blocking agent, administered at a dose of 500 mg four times a day, did not change the pharmacokinetics of levetiracetam 1000 mg twice daily. Cssmax of the metabolite, ucb L057, was approximately doubled in the presence of probenecid while the fraction of drug excreted unchanged in the urine remained the same. Renal clearance of ucb L057 in the presence of probenecid decreased 60%, probably related to competitive inhibition of tubular secretion of ucb L057. The effect of KEPPRA on probenecid was not studied.

Carcinogenesis, Mutagenesis, Impairment Of Fertility

Carcinogenesis

Rats were dosed with levetiracetam in the diet for 104 weeks at doses of 50, 300 and 1800 mg/kg/day. The highest dose corresponds to 6 times the maximum recommended daily human dose (MRHD) of 3000 mg on a mg/m^2 basis and it also provided systemic exposure (AUC) approximately 6 times that achieved in humans receiving the MRHD. There was no evidence of carcinogenicity. A study was conducted in which mice received levetiracetam in the diet for 80 weeks at doses of 60, 240 and 960 mg/kg/day (high dose is equivalent to 2 times the MRHD on a mg/m^2 or exposure basis). Although no evidence for carcinogenicity was seen, the potential for a carcinogenic response has not been fully evaluated in that species because adequate doses have not been studied.

Mutagenesis

Levetiracetam was not mutagenic in the Ames test or in mammalian cells in vitro in the Chinese hamster ovary/HGPRT locus assay. It was not clastogenic in an in vitro analysis of metaphase chromosomes obtained from Chinese hamster ovary cells or in an in vivo mouse micronucleus assay. The hydrolysis product and major human metabolite of levetiracetam (ucb L057) was not mutagenic in the Ames test or the in vitro mouse lymphoma assay.

Impairment Of Fertility

No adverse effects on male or female fertility or reproductive performance were observed in rats at doses up to 1800 mg/kg/day (approximately 6 times the maximum recommended human dose on a mg/m^2 or exposure basis).

Pregnancy

Pregnancy Category C

In animal studies, levetiracetam produced evidence of developmental toxicity at doses similar to or greater than human therapeutic doses.

Administration to female rats throughout pregnancy and lactation was associated with increased incidences of minor fetal skeletal abnormalities and retarded offspring growth pre- and/or postnatally at doses ≥350 mg/kg/day (approximately equivalent to the maximum recommended human dose of 3000 mg [MRHD] on a mg/m^2 basis) and with increased pup mortality and offspring behavioral alterations at a dose of 1800 mg/kg/day (6 times the MRHD on a mg/m^2 basis). The developmental no effect dose was 70 mg/kg/day (0.2 times the MRHD on a mg/m^2 basis). There was no overt maternal toxicity at the doses used in this study.

Treatment of pregnant rabbits during the period of organogenesis resulted in increased embryofetal mortality and increased incidences of minor fetal skeletal abnormalities at doses ≥600 mg/kg/day (approximately 4 times MRHD on a mg/m^2 basis) and in decreased fetal weights and increased incidences of fetal malformations at a dose of 1800 mg/kg/day (12 times the MRHD on a mg/m^2 basis). The developmental no effect dose was 200 mg/kg/day (1.3 times the MRHD on a mg/m^2 basis). Maternal toxicity was also observed at 1800 mg/kg/day.

When pregnant rats were treated during the period of organogenesis, fetal weights were decreased and the incidence of fetal skeletal variations was increased at a dose of 3600 mg/kg/day (12 times the MRHD). 1200 mg/kg/day (4 times the MRHD) was a developmental no effect dose. There was no evidence of maternal toxicity in this study.

Treatment of rats during the last third of gestation and throughout lactation produced no adverse developmental or maternal effects at doses of up to 1800 mg/kg/day (6 times the MRHD on a mg/m^2 basis).

There are no adequate and well-controlled studies in pregnant women. KEPPRA should be used during pregnancy only if the potential benefit justifies the potential risk to the fetus. As with other antiepileptic drugs, physiological changes during pregnancy may affect levetiracetam concentration. There have been reports of decreased levetiracetam concentration during pregnancy. Discontinuation of antiepileptic treatments may result in disease worsening, which can be harmful to the mother and the fetus.

Pregnancy Registries

To provide information regarding the effects of in utero exposure to KEPPRA, physicians are advised to recommend that pregnant patients taking KEPPRA enroll in the North American Antiepileptic Drug (NAAED) pregnancy registry. This can be done by calling the toll free number 1-888-233-2334, and must be done by the patients themselves. Information on the registry can also be found at the website http://www.aedpregnancyregistry.org/.

UCB, Inc. has established the UCB AED Pregnancy Registry to advance scientific knowledge about safety and outcomes associated with pregnant women being treated with all UCB antiepileptic drugs, including KEPPRA. To ensure broad program access and reach, either a healthcare provider or the patient can initiate enrollment in the UCB AED Pregnancy Registry by calling (888) 537-7734 (toll free).

Labor And Delivery

The effect of KEPPRA on labor and delivery in humans is unknown.

Nursing Mothers

Levetiracetam is excreted in breast milk. Because of the potential for serious adverse reactions in nursing infants from KEPPRA, a decision should be made whether to discontinue nursing or discontinue the drug, taking into account the importance of the drug to the mother.

Pediatric Use

Safety and effectiveness in patients below 4 years of age have not been established.

Studies of levetiracetam in juvenile rats (dosing from day 4 through day 52 of age) and dogs (dosing from week 3 through week 7 of age) at doses of up to 1800 mg/kg/day (approximately 7 and 24 times, respectively, the maximum recommended pediatric dose of 60 mg/kg/day on a mg/m^2 basis) did not indicate a potential for age-specific toxicity.

Geriatric Use

Of the total number of subjects in clinical studies of levetiracetam, 347 were 65 and over. No overall differences in safety were observed between these subjects and younger subjects. There were insufficient numbers of elderly subjects in controlled trials of epilepsy to adequately assess the effectiveness of KEPPRA in these patients.

A study in 16 elderly subjects (age 61-88 years) with oral administration of single dose and multiple twice-daily doses for 10 days showed no pharmacokinetic differences related to age alone.

Levetiracetam is known to be substantially excreted by the kidney, and the risk of adverse reactions to this drug may be greater in patients with impaired renal function. Because elderly patients are more likely to have decreased renal function, care should be taken in dose selection, and it may be useful to monitor renal function.

Use In Patients With Impaired Renal Function

Clearance of levetiracetam is decreased in patients with renal impairment and is correlated with creatinine clearance. Caution should be taken in dosing patients with moderate and severe renal impairment and in patients undergoing hemodialysis. The dosage should be reduced in patients with impaired renal function receiving KEPPRA and supplemental doses should be given to patients after dialysis (see CLINICAL PHARMACOLOGY and DOSAGE AND ADMINISTRATION, Adult Patients With Impaired Renal Function).

ADVERSE REACTIONS

The prescriber should be aware that the adverse event incidence figures in the following tables, obtained when KEPPRA was added to concurrent AED therapy, cannot be used to predict the frequency of adverse experiences in the course of usual medical practice where patient characteristics and other factors may differ from those prevailing during clinical studies. Similarly, the cited frequencies cannot be directly compared with figures obtained from other clinical investigations involving different treatments, uses, or investigators. An inspection of these frequencies, however, does provide the prescriber with one basis to estimate the relative contribution of drug and non-drug factors to the adverse event incidences in the population studied.

Partial Onset Seizures

In well-controlled clinical studies in adults with partial onset seizures, the most frequently reported adverse events associated with the use of KEPPRA in combination with other AEDs, not seen at an equivalent frequency among placebo-treated patients, were somnolence, asthenia, infection and dizziness. In the well-controlled pediatric clinical study in children 4 to 16 years of age with partial onset seizures, the adverse events most frequently reported with the use of KEPPRA in combination with other AEDs, not seen at an equivalent frequency among placebo-treated patients, were somnolence, accidental injury, hostility, nervousness, and asthenia.

Table 8 lists treatment-emergent adverse events that occurred in at least 1% of adult epilepsy patients treated with KEPPRA participating in placebo-controlled studies and were numerically more common than in patients treated with placebo. Table 9 lists treatment-emergent adverse events that occurred in at least 2% of pediatric epilepsy patients (ages 4-16 years) treated with KEPPRA participating in the placebo-controlled study and were numerically more common than in pediatric patients treated with placebo. In these studies, either KEPPRA or placebo was added to concurrent AED therapy. Adverse events were usually mild to moderate in intensity.

Table 8: Incidence (%) Of Treatment-Emergent Adverse Events In Placebo-Controlled, Add-On Studies In Adults Experiencing Partial Onset Seizures By Body System (Adverse Events Occurred In At Least 1% Of KEPPRA-Treated Patients And Occurred More Frequently Than Placebo-Treated Patients)
Body System/ Adverse Event | KEPPRA (N=769) % | Placebo (N=439) %
Body as a Whole
Asthenia | 15 | 9
Headache | 14 | 13
Infection | 13 | 8
Pain | 7 | 6
Digestive System
Anorexia | 3 | 2
Nervous System
Somnolence | 15 | 8
Dizziness | 9 | 4
Depression | 4 | 2
Nervousness | 4 | 2
Ataxia | 3 | 1
Vertigo | 3 | 1
Amnesia | 2 | 1
Anxiety | 2 | 1
Hostility | 2 | 1
Paresthesia | 2 | 1
Emotional Lability | 2 | 0
Respiratory System
Pharyngitis | 6 | 4
Rhinitis | 4 | 3
Cough Increased | 2 | 1
Sinusitis | 2 | 1
Special Senses
Diplopia | 2 | 1

Other events reported by at least 1% of adult KEPPRA-treated patients but as or more frequent in the placebo group were the following: abdominal pain, accidental injury, amblyopia, arthralgia, back pain, bronchitis, chest pain, confusion, constipation, convulsion, diarrhea, drug level increased, dyspepsia, ecchymosis, fever, flu syndrome, fungal infection, gastroenteritis, gingivitis, grand mal convulsion, insomnia, nausea, otitis media, rash, thinking abnormal, tremor, urinary tract infection, vomiting and weight gain.

Table 9: Incidence (%) Of Treatment-Emergent Adverse Events In A Placebo-Controlled, Add-On Study In Pediatric Patients Ages 4-16 Years Experiencing Partial Onset Seizures By Body System (Adverse Events Occurred In At Least 2% Of KEPPRA-Treated Patients And Occurred More Frequently Than Placebo-Treated Patients)
Body System/ Adverse Event | KEPPRA (N=101) % | Placebo (N=97) %
Body as a Whole
Accidental Injury | 17 | 10
Asthenia | 9 | 3
Pain | 6 | 3
Flu Syndrome | 3 | 2
Face Edema | 2 | 1
Neck Pain | 2 | 1
Viral Infection | 2 | 1
Digestive System
Vomiting | 15 | 13
Anorexia | 13 | 8
Diarrhea | 8 | 7
Gastroenteritis | 4 | 2
Constipation | 3 | 1
Hemic and Lymphatic System
Ecchymosis | 4 | 1
Metabolic and Nutritional
Dehydration | 2 | 1
Nervous System
Somnolence | 23 | 11
Hostility | 12 | 6
Nervousness | 10 | 2
Personality Disorder | 8 | 7
Dizziness | 7 | 2
Emotional Lability | 6 | 4
Agitation | 6 | 1
Depression | 3 | 1
Vertigo | 3 | 1
Reflexes Increased | 2 | 1
Confusion | 2 | 0
Respiratory System
Rhinitis | 13 | 8
Cough Increased | 11 | 7
Pharyngitis | 10 | 8
Asthma | 2 | 1
Skin and Appendages
Pruritus | 2 | 0
Skin Discoloration | 2 | 0
Vesiculobullous Rash | 2 | 0
Special Senses
Conjunctivitis | 3 | 2
Amblyopia | 2 | 0
Ear Pain | 2 | 0
Urogenital System
Albuminuria | 4 | 0
Urine Abnormality | 2 | 1

Other events occurring in at least 2% of pediatric KEPPRA-treated patients but as or more frequent in the placebo group were the following: abdominal pain, allergic reaction, ataxia, convulsion, epistaxis, fever, headache, hyperkinesia, infection, insomnia, nausea, otitis media, rash, sinusitis, status epilepticus (not otherwise specified), thinking abnormal, tremor, and urinary incontinence.

Myoclonic Seizures

Although the pattern of adverse events in this study seems somewhat different from that seen in patients with partial seizures, this is likely due to the much smaller number of patients in this study compared to partial seizure studies. The adverse event pattern for patients with JME is expected to be essentially the same as for patients with partial seizures.

In the well-controlled clinical study that included both adolescent (12 to 16 years of age) and adult patients with myoclonic seizures, the most frequently reported adverse events associated with the use of KEPPRA in combination with other AEDs, not seen at an equivalent frequency among placebo-treated patients, were somnolence, neck pain, and pharyngitis.

Table 10 lists treatment-emergent adverse events that occurred in at least 5% of juvenile myoclonic epilepsy patients experiencing myoclonic seizures treated with KEPPRA and were numerically more common than in patients treated with placebo. In this study, either KEPPRA or placebo was added to concurrent AED therapy. Adverse events were usually mild to moderate in intensity.

Table 10: Incidence (%) Of Treatment-Emergent Adverse Events In A Placebo-Controlled, Add-On Study In Patients 12 Years Of Age And Older With Myoclonic Seizures By Body System (Adverse Events Occurred In At Least 5% Of KEPPRA-Treated Patients And Occurred More Frequently Than Placebo-Treated Patients)
Body System / MedDRA preferred term | KEPPRA (N=60) % | Placebo (N=60) %
Ear and labyrinth disorders
Vertigo | 5 | 3
Infections and infestations
Pharyngitis | 7 | 0
Influenza | 5 | 2
Musculoskeletal and connective tissue disorders
Neck pain | 8 | 2
Nervous system disorders
Somnolence | 12 | 2
Psychiatric disorders
Depression | 5 | 2

Other events occurring in at least 5% of KEPPRA-treated patients with myoclonic seizures but as or more frequent in the placebo group were the following: fatigue and headache.

Primary Generalized Tonic-Clonic Seizures

Although the pattern of adverse events in this study seems somewhat different from that seen in patients with partial seizures, this is likely due to the much smaller number of patients in this study compared to partial seizure studies. The adverse event pattern for patients with PGTC seizures is expected to be essentially the same as for patients with partial seizures.

In the well-controlled clinical study that included patients 4 years of age and older with primary generalized tonic-clonic (PGTC) seizures, the most frequently reported adverse event associated with the use of KEPPRA in combination with other AEDs, not seen at an equivalent frequency among placebo-treated patients, was nasopharyngitis.

Table 11 lists treatment-emergent adverse events that occurred in at least 5% of idiopathic generalized epilepsy patients experiencing PGTC seizures treated with KEPPRA and were numerically more common than in patients treated with placebo. In this study, either KEPPRA or placebo was added to concurrent AED therapy. Adverse events were usually mild to moderate in intensity.

Table 11: Incidence (%) Of Treatment-Emergent Adverse Events In A Placebo-Controlled, Add-On Study In Patients 4 Years Of Age And Older With PGTC Seizures By MedDRA System Organ Class (Adverse Events Occurred In At Least 5% Of KEPPRA-Treated Patients And Occurred More Frequently Than Placebo-Treated Patients)
MedDRA System Organ Class/ Preferred Term | KEPPRA (N=79) % | Placebo (N=84) %
Gastrointestinal disorders
Diarrhea | 8 | 7
General disorders and administration site conditions
Fatigue | 10 | 8
Infections and infestations
Nasopharyngitis | 14 | 5
Psychiatric disorders
Irritability | 6 | 2
Mood swings | 5 | 1

Other events occurring in at least 5% of KEPPRA-treated patients with PGTC seizures but as or more frequent in the placebo group were the following: dizziness, headache, influenza, and somnolence.

Time Course Of Onset Of Adverse Events For Partial Onset Seizures

Of the most frequently reported adverse events in adults experiencing partial onset seizures, asthenia, somnolence and dizziness appeared to occur predominantly during the first 4 weeks of treatment with KEPPRA.

Discontinuation Or Dose Reduction In Well-Controlled Clinical Studies

Partial Onset Seizures

In well-controlled adult clinical studies, 15.0% of patients receiving KEPPRA and 11.6% receiving placebo either discontinued or had a dose reduction as a result of an adverse event. Table 12 lists the most common (>1%) adverse events that resulted in discontinuation or dose reduction.

Table 12: Adverse Events That Most Commonly Resulted In Discontinuation Or Dose Reduction In Placebo-Controlled Studies In Adult Patients Experiencing Partial Onset Seizures
 | Number (%)
 | KEPPRA (N=769) | Placebo (N=439)
Asthenia | 10 (1.3%) | 3 (0.7%)
Convulsion | 23 (3.0%) | 15 (3.4%)
Dizziness | 11 (1.4%) | 0
Rash | 0 | 5 (1.1%)
Somnolence | 34 (4.4%) | 7 (1.6%)

In the well-controlled pediatric clinical study, 16.8% of patients receiving KEPPRA and 20.6% receiving placebo either discontinued or had a dose reduction as a result of an adverse event. The adverse events most commonly associated (≥3% in patients receiving KEPPRA) with discontinuation or dose reduction in the well-controlled study are presented in Table 13.

Table 13: Adverse Events Most Commonly Associated With Discontinuation Or Dose Reduction In The Placebo-Controlled Study In Pediatric Patients Ages 4-16 Years Experiencing Partial Onset Seizures
 | Number (%)
 | KEPPRA (N=101) | Placebo (N=97)
Asthenia | 3 (3.0%) | 0
Hostility | 7 (6.9%) | 2 (2.1%)
Somnolence | 3 (3.0%) | 3 (3.1%)

Myoclonic Seizures

In the placebo-controlled study, 8.3% of patients receiving KEPPRA and 1.7% receiving placebo either discontinued or had a dose reduction as a result of an adverse event. The adverse events that led to discontinuation or dose reduction in the well-controlled study are presented in Table 14.

Table 14: Adverse Events That Resulted In Discontinuation Or Dose Reduction In The Placebo-Controlled Study In Patients With Juvenile Myoclonic Epilepsy
Body System/ MedDRA preferred term | KEPPRA (N=60) n (%) | Placebo (N=60) n (%)
Anxiety | 2 (3.3%) | 1 (1.7%)
Depressed mood | 1 (1.7%) | 0
Depression | 1 (1.7%) | 0
Diplopia | 1 (1.7%) | 0
Hypersomnia | 1 (1.7%) | 0
Insomnia | 1 (1.7%) | 0
Irritability | 1 (1.7%) | 0
Nervousness | 1 (1.7%) | 0
Somnolence | 1 (1.7%) | 0

Primary Generalized Tonic-Clonic Seizures

In the placebo-controlled study, 5.1% of patients receiving KEPPRA and 8.3% receiving placebo either discontinued or had a dose reduction during the treatment period as a result of a treatment-emergent adverse event.

This study was too small to adequately characterize the adverse events leading to discontinuation. It is expected that the adverse events that would lead to discontinuation in this population would be similar to those resulting in discontinuation in other epilepsy trials (see tables 12 - 14).

Comparison Of Gender, Age And Race

The overall adverse experience profile of KEPPRA was similar between females and males. There are insufficient data to support a statement regarding the distribution of adverse experience reports by age and race.

Postmarketing Experience

In addition to the adverse experiences listed above, the following have been reported in patients receiving marketed KEPPRA worldwide. The listing is alphabetized: abnormal liver function test, hepatic failure, hepatitis, leukopenia, neutropenia, pancreatitis, pancytopenia (with bone marrow suppression identified in some of these cases), thrombocytopenia, and weight loss. Alopecia has been reported with KEPPRA use; recovery was observed in majority of cases where KEPPRA was discontinued. These adverse experiences have not been listed above, and data are insufficient to support an estimate of their incidence or to establish causation.

DRUG ABUSE AND DEPENDENCE

The abuse and dependence potential of KEPPRA has not been evaluated in human studies.

OVERDOSAGE

Signs, Symptoms And Laboratory Findings Of Acute Overdosage In Humans

The highest known dose of KEPPRA received in the clinical development program was 6000 mg/day. Other than drowsiness, there were no adverse events in the few known cases of overdose in clinical trials. Cases of somnolence, agitation, aggression, depressed level of consciousness, respiratory depression and coma were observed with KEPPRA overdoses in postmarketing use.

Treatment Or Management Of Overdose

There is no specific antidote for overdose with KEPPRA. If indicated, elimination of unabsorbed drug should be attempted by emesis or gastric lavage; usual precautions should be observed to maintain airway. General supportive care of the patient is indicated including monitoring of vital signs and observation of the patient's clinical status. A Certified Poison Control Center should be contacted for up to date information on the management of overdose with KEPPRA.

Hemodialysis

Standard hemodialysis procedures result in significant clearance of levetiracetam (approximately 50% in 4 hours) and should be considered in cases of overdose. Although hemodialysis has not been performed in the few known cases of overdose, it may be indicated by the patient's clinical state or in patients with significant renal impairment.

DOSAGE AND ADMINISTRATION

KEPPRA is indicated as adjunctive treatment of partial onset seizures in adults and children 4 years of age and older with epilepsy.

KEPPRA is indicated as adjunctive therapy in the treatment of myoclonic seizures in adults and adolescents 12 years of age and older with juvenile myoclonic epilepsy.

KEPPRA is indicated as adjunctive therapy in the treatment of primary generalized tonic-clonic seizures in adults and children 6 years of age and older with idiopathic generalized epilepsy.

Partial Onset Seizures

Adults 16 Years And Older

In clinical trials, daily doses of 1000 mg, 2000 mg, and 3000 mg, given as twice-daily dosing, were shown to be effective. Although in some studies there was a tendency toward greater response with higher dose (see CLINICAL STUDIES), a consistent increase in response with increased dose has not been shown.

Treatment should be initiated with a daily dose of 1000 mg/day, given as twice-daily dosing (500 mg BID). Additional dosing increments may be given (1000 mg/day additional every 2 weeks) to a maximum recommended daily dose of 3000 mg. Doses greater than 3000 mg/day have been used in open-label studies for periods of 6 months and longer. There is no evidence that doses greater than 3000 mg/day confer additional benefit.

Pediatric Patients Ages 4 To <16 Years

Treatment should be initiated with a daily dose of 20 mg/kg in 2 divided doses (10 mg/kg BID). The daily dose should be increased every 2 weeks by increments of 20 mg/kg to the recommended daily dose of 60 mg/kg (30 mg/kg BID). If a patient cannot tolerate a daily dose of 60 mg/kg, the daily dose may be reduced. In the clinical trial, the mean daily dose was 52 mg/kg. Patients with body weight ≤ 20 kg should be dosed with oral solution. Patients with body weight above 20 kg can be dosed with either tablets or oral solution. Table 15 below provides a guideline for tablet dosing based on weight during titration to 60 mg/kg/day. Only whole tablets should be administered.

KEPPRA is given orally with or without food.

Table 15: KEPPRA Tablet Weight-Based Dosing Guide For Children
 | Daily Dose
Patient Weight | 20 mg/kg/day (BID dosing) | 40 mg/kg/day (BID dosing) | 60 mg/kg/day (BID dosing)
20.1-40 kg | 500 mg/day (1 x 250 mg tablet BID) | 1000 mg/day (1 x 500 mg tablet BID) | 1500 mg/day (1 x 750 mg tablet BID)
>40 kg | 1000 mg/day (1 x 500 mg tablet BID) | 2000 mg/day (2 x 500 mg tablets BID) | 3000 mg/day (2 x 750 mg tablets BID)

The following calculation should be used to determine the appropriate daily dose of oral solution for pediatric patients based on a daily dose of 20 mg/kg/day, 40 mg/kg/day or 60 mg/kg/day:

Total daily dose (mL/day) = | Daily dose (mg/kg/day) x patient weight (kg)
Total daily dose (mL/day) = | - - - - - - - - - - - - - - - - - - - - - - - - - - - - - - - - - - -
Total daily dose (mL/day) = | 100 mg/mL

A household teaspoon or tablespoon is not an adequate measuring device. It is recommended that a calibrated measuring device be obtained and used. Healthcare providers should recommend a device that can measure and deliver the prescribed dose accurately, and provide instructions for measuring the dosage.

Myoclonic Seizures In Patients 12 Years Of Age And Older With Juvenile Myoclonic Epilepsy

Treatment should be initiated with a dose of 1000 mg/day, given as twice-daily dosing (500 mg BID). Dosage should be increased by 1000 mg/day every 2 weeks to the recommended daily dose of 3000 mg. The effectiveness of doses lower than 3000 mg/day has not been studied.

Primary Generalized Tonic-Clonic Seizures

Adults 16 Years And Older

Treatment should be initiated with a dose of 1000 mg/day, given as twice-daily dosing (500 mg BID). Dosage should be increased by 1000 mg/day every 2 weeks to the recommended daily dose of 3000 mg. The effectiveness of doses lower than 3000 mg/day has not been adequately studied.

Pediatric Patients Ages 6 To <16 Years

Treatment should be initiated with a daily dose of 20 mg/kg in 2 divided doses (10 mg/kg BID). The daily dose should be increased every 2 weeks by increments of 20 mg/kg to the recommended daily dose of 60 mg/kg (30 mg/kg BID). The effectiveness of doses lower than 60 mg/kg/day has not been adequately studied. Patients with body weight ≤ 20 kg should be dosed with oral solution. Patients with body weight above 20 kg can be dosed with either tablets or oral solution. See Table 14 for tablet dosing based on weight during titration to 60 mg/kg/day. Only whole tablets should be administered.

Adult Patients With Impaired Renal Function

KEPPRA dosing must be individualized according to the patient's renal function status. Recommended doses and adjustment for dose for adults are shown in Table 16. To use this dosing table, an estimate of the patient's creatinine clearance (CLcr) in mL/min is needed. CLcr in mL/min may be estimated from serum creatinine (mg/dL) determination using the following formula:

CLcr = | [140-age (years)] x weight (kg) | (x 0.85 for female patients)
CLcr = | - - - - - - - - - - - - - - - - - - - - - - | (x 0.85 for female patients)
CLcr = | 72 x serum creatinine (mg/dL) | (x 0.85 for female patients)

Table 16: Dosing Adjustment Regimen For Adult Patients With Impaired Renal Function
Group | Creatinine Clearance (mL/min) | Dosage (mg) | Frequency
Normal | > 80 | 500 to 1,500 | Every 12 h
Mild | 50 – 80 | 500 to 1,000 | Every 12 h
Moderate | 30 – 50 | 250 to 750 | Every 12 h
Severe | < 30 | 250 to 500 | Every 12 h
ESRD patients using dialysis | ---- | 500 to 1,000 | ^1Every 24 h
^1 Following dialysis, a 250 to 500 mg supplemental dose is recommended.

HOW SUPPLIED

KEPPRA 250 mg tablets are blue, oblong-shaped, scored, film-coated tablets debossed with "ucb 250" on one side. They are supplied in white HDPE bottles containing 120 tablets (NDC 50474-594-40).

KEPPRA 500 mg tablets are yellow, oblong-shaped, scored, film-coated tablets debossed with "ucb 500" on one side. They are supplied in white HDPE bottles containing 120 tablets (NDC 50474-595-40).

KEPPRA 750 mg tablets are orange, oblong-shaped, scored, film-coated tablets debossed with "ucb 750" on one side. They are supplied in white HDPE bottles containing 120 tablets (NDC 50474-596-40).

KEPPRA 1000 mg tablets are white, oblong-shaped, scored, film-coated tablets debossed with "ucb 1000" on one side. They are supplied in white HDPE bottles containing 60 tablets (NDC 50474-597-66).

KEPPRA 100 mg/mL oral solution is a clear, colorless, grape-flavored liquid. It is supplied in 16 fl. oz. white HDPE bottles (NDC 50474-001-48).

Storage

Store at 25°C (77°F); excursions permitted to 15-30°C (59-86°F) [see USP Controlled Room Temperature].

For Medical Information

Contact: Medical Affairs Department
Phone: (866) 822-0068
Fax: (770) 970-8859

KEPPRA Tablets and KEPPRA Oral Solution
Manufactured for
UCB, Inc.
Smyrna, GA 30080

KEPPRA is a registered trademark of the UCB Group of companies.
© 2009, UCB, Inc., Smyrna, GA 30080. All rights reserved. Printed in the U.S.A.

Rev. 29E 04/2009

MEDICATION GUIDE

KEPPRA® (KEPP-ruh) (levetiracetam)
tablets and oral solution

Read this Medication Guide before you start taking KEPPRA and each time you get a refill. There may be new information. This information does not take the place of talking to your healthcare provider about your medical condition or treatment.

What is the most important information I should know about KEPPRA?

Like other antiepileptic drugs, KEPPRA may cause suicidal thoughts or actions in a very small number of people, about 1 in 500 people taking it.

Call a healthcare provider right away if you have any of these symptoms, especially if they are new, worse, or worry you:

- thoughts about suicide or dying
- attempts to commit suicide
- new or worse depression
- new or worse anxiety
- feeling agitated or restless
- panic attacks
- trouble sleeping (insomnia)
- new or worse irritability
- acting aggressive, being angry, or violent
- acting on dangerous impulses
- an extreme increase in activity and talking (mania)
- other unusual changes in behavior or mood

Do not stop KEPPRA without first talking to a healthcare provider.

- Stopping KEPPRA suddenly can cause serious problems. Stopping a seizure medicine suddenly can cause seizures that will not stop (status epilepticus).
- Suicidal thoughts or actions can be caused by things other than medicines. If you have suicidal thoughts or actions, your healthcare provider may check for other causes.

How can I watch for early symptoms of suicidal thoughts and actions?

- Pay attention to any changes, especially sudden changes, in mood, behaviors, thoughts, or feelings.
- Keep all follow-up visits with your healthcare provider as scheduled.
- Call your healthcare provider between visits as needed, especially if you are worried about symptoms.

What is KEPPRA?

KEPPRA is a prescription medicine taken by mouth that is used with other medicines to treat:

- partial onset seizures in people 4 years of age and older with epilepsy
- myoclonic seizures in people 12 years of age and older with juvenile myoclonic epilepsy
- primary generalized tonic-clonic seizures in people 6 years of age and older with certain types of generalized epilepsy.

It is not known if KEPPRA is safe or effective in children under 4 years of age.

Before taking your medicine, make sure you have received the correct medicine. Compare the name above with the name on your bottle and the appearance of your medicine with the description of KEPPRA provided below. Tell your pharmacist immediately if you think you have been given the wrong medicine.

250 mg KEPPRA tablets are blue, oblong-shaped, scored, film-coated tablets marked with "ucb 250" on one side.

500 mg KEPPRA tablets are yellow, oblong-shaped, scored, film-coated tablets marked with "ucb 500" on one side.

750 mg KEPPRA tablets are orange, oblong-shaped, scored, film-coated tablets marked with "ucb 750" on one side.

1000 mg KEPPRA tablets are white, oblong-shaped, scored, film-coated tablets marked with "ucb 1000" on one side.

KEPPRA oral solution is a clear, colorless, grape-flavored liquid.

What should I tell my healthcare provider before starting KEPPRA?

Before taking KEPPRA, tell your healthcare provider about all of your medical conditions, including if you:

- have or have had depression, mood problems or suicidal thoughts or behavior
- have kidney problems
- are pregnant or planning to become pregnant. It is not known if KEPPRA will harm your unborn baby. You and your healthcare provider will have to decide if you should take KEPPRA while you are pregnant. If you become pregnant while taking KEPPRA, talk to your healthcare provider about registering with the North American Antiepileptic Drug Pregnancy Registry. You can enroll in this registry by calling 1-888-233-2334. You can also enroll in the UCB AED Pregnancy Registry by calling 1-888-537-7734. The purpose of these registries is to collect information about the safety of KEPPRA and other antiepileptic medicine during pregnancy.
- are breast feeding. KEPPRA can pass into your milk and may harm your baby. You and your healthcare provider should discuss whether you should take KEPPRA or breast feed; you should not do both.

Tell your healthcare provider about all the medicines you take, including prescription and nonprescription medicines, vitamins, and herbal supplements. Do not start a new medicine without first talking with your healthcare provider.

Know the medicines you take. Keep a list of them to show your healthcare provider and pharmacist each time you get a new medicine.

How should I take KEPPRA?

Take KEPPRA exactly as prescribed.

- Your healthcare provider will tell you how much KEPPRA to take and when to take it. KEPPRA is usually taken twice a day. Take KEPPRA at the same times each day.
- Your healthcare provider may change your dose. Do not change your dose without talking to your healthcare provider.
- Take KEPPRA with or without food.
- Swallow the tablets whole. Do not chew or crush tablets. Ask your healthcare provider for KEPPRA oral solution if you cannot swallow tablets.
- If your healthcare provider has prescribed KEPPRA oral solution, be sure to ask your pharmacist for a medicine dropper or medicine cup to help you measure the correct amount of KEPPRA oral solution. Do not use a household teaspoon. Ask your pharmacist for instructions on how to use the measuring device the right way.
- If you miss a dose of KEPPRA, take it as soon as you remember. If it is almost time for your next dose, just skip the missed dose. Take the next dose at your regular time. Do not take two doses at the same time.
- If you take too much KEPPRA, call your local Poison Control Center or go to the nearest emergency room right away.

What should I avoid while taking KEPPRA?

Do not drive, operate machinery or do other dangerous activities until you know how KEPPRA affects you. KEPPRA may make you dizzy or sleepy.

What are the possible side effects of KEPPRA?

- See "What is the most important information I should know about KEPPRA?"

KEPPRA can cause serious side effects.

Call your healthcare provider right away if you have any of these symptoms:

- mood and behavior changes such as aggression, agitation, anger, anxiety, apathy, mood swings, depression, hostility, and irritability. A few people may get psychotic symptoms such as hallucinations (seeing or hearing things that are really not there), delusions (false or strange thoughts or beliefs) and unusual behavior.
- extreme sleepiness, tiredness, and weakness
- problems with muscle coordination (problems walking and moving)

The most common side effects seen in people who take KEPPRA include:

- sleepiness
- weakness
- dizziness
- infection

The most common side effects seen in children who take KEPPRA include, in addition to those listed above:

- accidental injury
- irritability
- hostility

These side effects can happen at any time but happen more often within the first 4 weeks of treatment except for infection.

Tell your healthcare provider if you have any side effect that bothers you or that does not go away.

These are not all the possible side effects of KEPPRA. For more information, ask your healthcare provider or pharmacist.

Call your doctor for medical advice about side effects. You may report side effects to FDA at 1-800-FDA-1088.

How should I store KEPPRA?

- Store KEPPRA at room temperature, 59°F to 86°F (15°C to 30°C) away from heat and light.
- Keep KEPPRA and all medicines out of the reach of children.

General information about KEPPRA.

Medicines are sometimes prescribed for purposes other than those listed in a Medication Guide. Do not use KEPPRA for a condition for which it was not prescribed. Do not give KEPPRA to other people, even if they have the same symptoms that you have. It may harm them.

This Medication Guide summarizes the most important information about KEPPRA. If you would like more information, talk with your healthcare provider. You can ask your pharmacist or healthcare provider for information about KEPPRA that is written for health professionals. You can also get information about KEPPRA at www.keppra.com or call 1-866-822-0068.

What are the ingredients of KEPPRA?

KEPPRA tablet active ingredient: levetiracetam

Inactive ingredients: colloidal silicon dioxide, croscarmellose sodium, magnesium stearate, polyethylene glycol 3350, polyethylene glycol 6000, polyvinyl alcohol, talc, titanium dioxide, and additional agents listed below:

250 mg tablets: FD&C Blue #2/indigo carmine aluminum lake

500 mg tablets: iron oxide yellow

750 mg tablets: FD&C yellow #6/sunset yellow FCF aluminum lake, iron oxide red

KEPPRA oral solution active ingredient: levetiracetam

Inactive ingredients: ammonium glycyrrhizinate, citric acid monohydrate, glycerin, maltitol solution, methylparaben, potassium acesulfame, propylparaben, purified water, sodium citrate dihydrate and natural and artificial flavor.

KEPPRA does not contain lactose or gluten. KEPPRA oral solution does contain carbohydrates. The liquid is dye-free.

Rx Only

This Medication Guide has been approved by the US Food and Drug Administration.

Distributed by
UCB, Inc.
Smyrna, GA 30080

KEPPRA is a registered trademark of the UCB Group of companies
©2009, UCB, Inc., Smyrna, GA 30080
All rights reserved.
Printed in the U.S.A.

Rev. 1E 04/2009